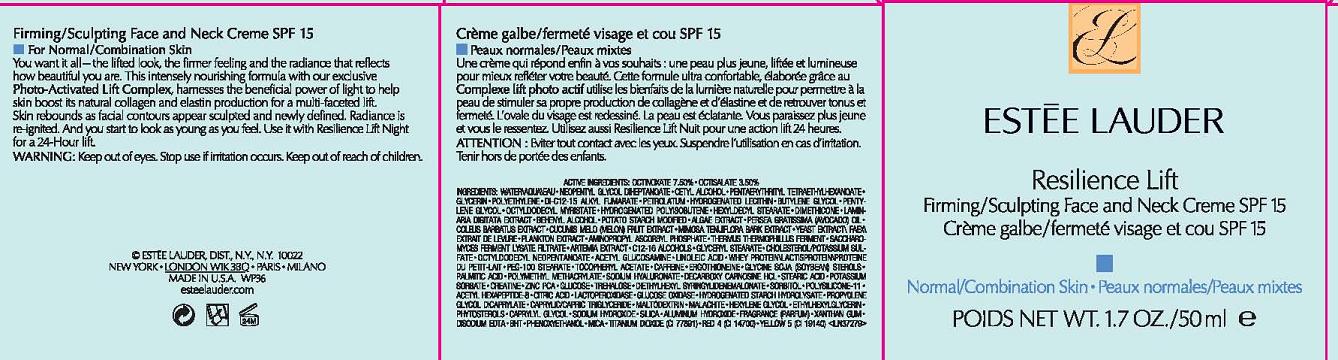 DRUG LABEL: RESILIENCE LIFT
NDC: 11559-011 | Form: CREAM
Manufacturer: ESTEE LAUDER INC
Category: otc | Type: HUMAN OTC DRUG LABEL
Date: 20110419

ACTIVE INGREDIENTS: OCTINOXATE 7.5 mL/100 mL; OCTISALATE 3.5 mL/100 mL
INACTIVE INGREDIENTS: WATER; CETYL ALCOHOL; GLYCERIN; HIGH DENSITY POLYETHYLENE; PETROLATUM; LECITHIN, SOYBEAN; BUTYLENE GLYCOL; PENTYLENE GLYCOL; HYDROGENATED SOYBEAN LECITHIN; DIMETHICONE; LAMINARIA SACCHARINA; AVOCADO OIL; CUCUMBER; SEAWEED; SACCHAROMYCES LYSATE; GLYCERYL MONOSTEARATE; CHOLESTEROL; GLUCOSAMINE; LINOLEIC ACID; .ALPHA.-TOCOPHEROL ACETATE, DL-; CAFFEINE; HYALURONATE SODIUM; POTASSIUM SORBATE; CREATINE; TREHALOSE; SORBITOL; CITRIC ACID MONOHYDRATE; HEXYLENE GLYCOL; CAPRYLYL GLYCOL; SILICON DIOXIDE; XANTHAN GUM; EDETATE DISODIUM; BUTYLATED HYDROXYTOLUENE; PHENOXYETHANOL; TITANIUM DIOXIDE; FD&C YELLOW NO. 5

ACTIVE INGREDIENT: 7.5% OCTINOXATE

INACTIVE INGREDIENT

INACTIVE INGREDIENTS: WATER [] NEOPENTYL GLYCOL DIHEPTANOATE [] CETYL ALCOHOL [] PENTAERYTHRITYL TETRAETHYLHEXANOATE [] GLYCERIN [] POLYETHYLENE [] DI-C12-15 ALKYL FUMARATE [] PETROLATUM [] HYDROGENATED LECITHIN [] BUTYLENE GLYCOL [] PENTYLENE GLYCOL [] OCTYLDODECYL MYRISTATE [] HYDROGENATED POLYISOBUTENE [] HEXYLDECYL STEARATE [] DIMETHICONE [] LAMINARIA DIGITATA EXTRACT [] BEHENYL ALCOHOL [] POTATO STARCH MODIFIED [] ALGAE EXTRACT [] PERSEA GRATISSIMA (AVOCADO) OIL [] COLEUS BARBATUS EXTRACT [] CUCUMIS MELO (MELON) FRUIT EXTRACT [] MIMOSA TENUIFLORA BARK EXTRACT [] YEAST EXTRACT\FAEX\EXTRAIT DE LEVURE [] PLANKTON EXTRACT [] AMINOPROPYL ASCORBYL PHOSPHATE [] THERMUS THERMOPHILLUS FERMENT [] SACCHAROMYCES FERMENT LYSATE FILTRATE [] ARTEMIA EXTRACT [] C12-16 ALCOHOLS [] GLYCERYL STEARATE [] CHOLESTEROL/POTASSIUM SULFATE [] OCTYLDODECYL NEOPENTANOATE [] ACETYL GLUCOSAMINE [] LINOLEIC ACID [] WHEY PROTEIN [] PEG-100 STEARATE [] TOCOPHERYL ACETATE [] CAFFEINE [] ERGOTHIONEINE [] GLYCINE SOJA (SOYBEAN) STEROLS [] PALMITIC ACID [] POLYMETHYL METHACRYLATE [] SODIUM HYALURONATE [] DECARBOXY CARNOSINE HCL [] STEARIC ACID [] POTASSIUM SORBATE [] CREATINE [] ZINC PCA [] GLUCOSE [] TREHALOSE [] DIETHYLHEXYL SYRINGYLIDENEMALONATE [] SORBITOL [] POLYSILICONE-11 [] ACETYL HEXAPEPTIDE-8 [] CITRIC ACID [] LACTOPEROXIDASE [] GLUCOSE OXIDASE [] HYDROGENATED STARCH HYDROLYSATE [] PROPYLENE GLYCOL DICAPRYLATE [] CAPRYLIC/CAPRIC TRIGLYCERIDE [] MALTODEXTRIN [] MALACHITE [] HEXYLENE GLYCOL [] ETHYLHEXYLGLYCERIN [] PHYTOSTEROLS [] CAPRYLYL GLYCOL [] SODIUM HYDROXIDE [] SILICA [] ALUMINA [] FRAGRANCE (PARFUM) [] XANTHAN GUM [] DISODIUM EDTA [] BHT [] PHENOXYETHANOL [] MICA [] TITANIUM DIOXIDE (CI 77891) [] RED 4 (CI 14700) [] YELLOW 5 (CI 19140)

WARNINGS

WARNING: KEEP OUT OF EYES. STOP USE IF IRRITATION OCCURS.

KEEP OUT OF REACH OF CHILDREN.

PACKAGE LABEL

PRINCIPAL DISPLAY PANEL:

ESTEE LAUDER
RESILIENCE LIFT
FIRMING/SCULPTING FACE AND NECK CREME
SPF 15
NORMAL/COMBINATION SKIN
NET WT. 1.7 OZ/ 50 ML
ESTEE LAUDER DISTR
NEW YORK, NY 10022